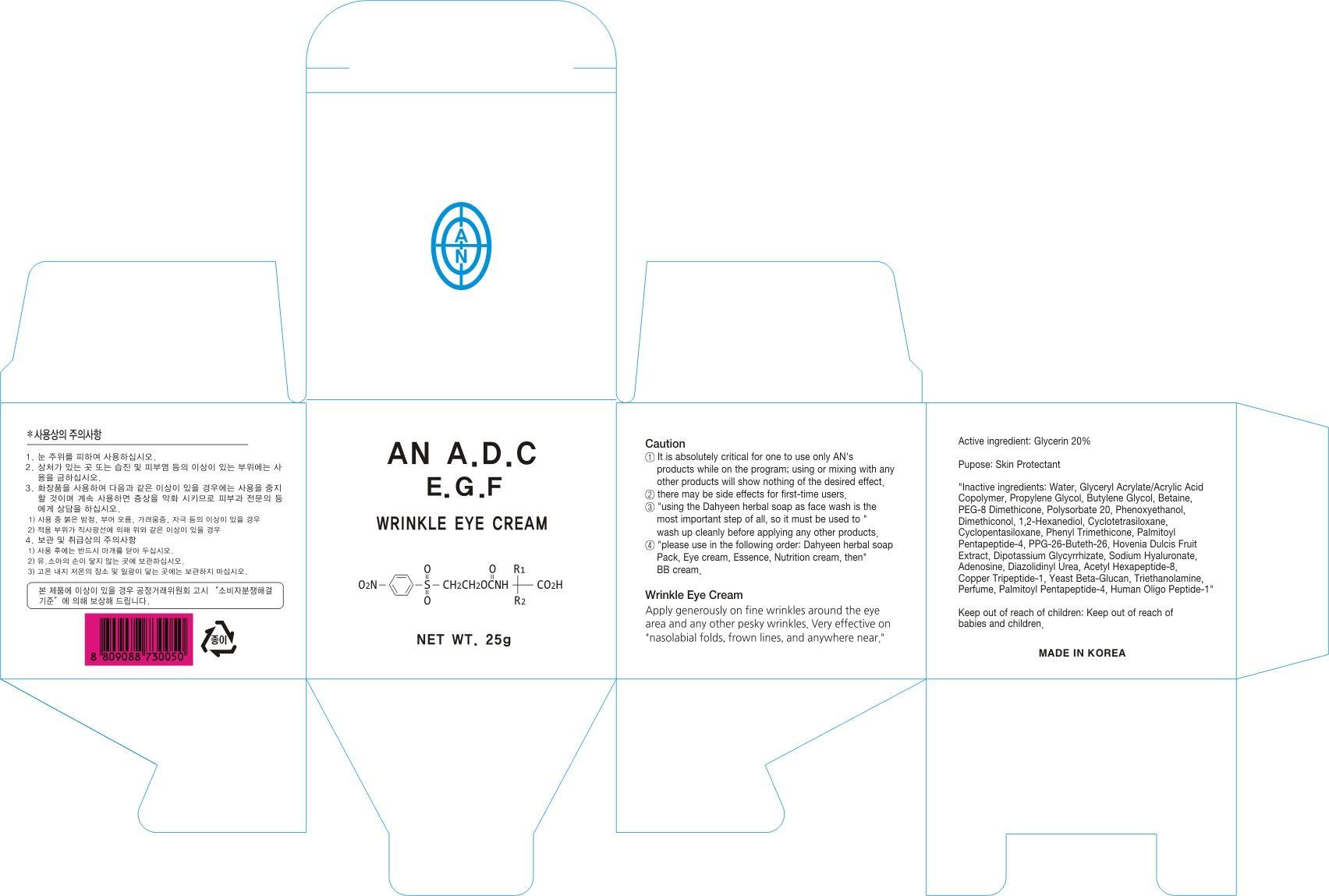 DRUG LABEL: AN ADC EGF WRINKLE EYE
NDC: 69153-030 | Form: CREAM
Manufacturer: AN Co Ltd.
Category: otc | Type: HUMAN OTC DRUG LABEL
Date: 20140929

ACTIVE INGREDIENTS: Glycerin 5 g/25 g
INACTIVE INGREDIENTS: Water; Propylene Glycol

ACTIVE INGREDIENT

Active ingredient: Glycerin 20%

INACTIVE INGREDIENT

Inactive ingredients: Water, Glyceryl Acrylate/Acrylic Acid Copolymer, Propylene Glycol, Butylene Glycol, Betaine, PEG-8 Dimethicone, Polysorbate 20, Phenoxyethanol, Dimethiconol, 1,2-Hexanediol, Cyclotetrasiloxane, Cyclopentasiloxane, Phenyl Trimethicone, Palmitoyl Pentapeptide-4, PPG-26-Buteth-26, Hovenia Dulcis Fruit Extract, Dipotassium Glycyrrhizate, Sodium Hyaluronate, Adenosine, Diazolidinyl Urea, Acetyl Hexapeptide-8, Copper Tripeptide-1, Yeast Beta-Glucan, Triethanolamine, Perfume, Palmitoyl Pentapeptide-4, Human Oligo Peptide-1

PURPOSE

Purpose: Skin Protectant

Caution

1. It is absolutely critical for one to use only AN's products while on the program; using or mixing with any other products will show nothing of the desired effect.
2. There may be side effects for first-time users.
3. Using the Dahyeen herbal soap as face wash is the most important step of all, so it must be used to wash up cleanly before applying any other products.
4. Please use in the following order: Dahyeen herbal soap, Pack, Eye cream, Essence, Nutrition cream, then BB cream.

Keep out of reach of children: Keep out of reach of babies and children.

INDICATIONS & USAGE

Apply generously on fine wrinkles around the eye area and any other pesky wrinkles. Very effective on nasolabial folds, frown lines, and anywhere near.

DOSAGE & ADMINISTRATION

Apply generously on fine wrinkles around the eye area and any other pesky wrinkles. Very effective on nasolabial folds, frown lines, and anywhere near.